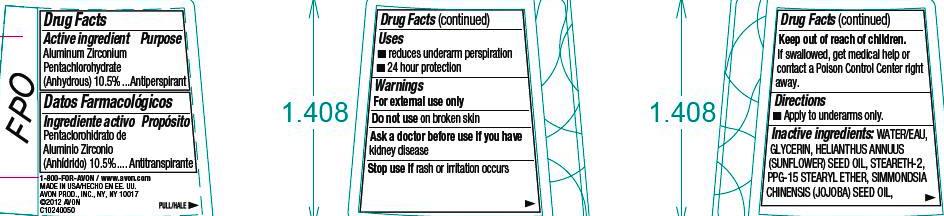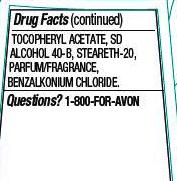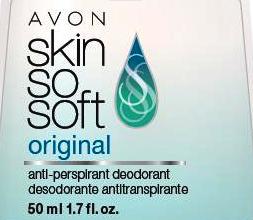 DRUG LABEL: Skin So Soft 
NDC: 10096-0275 | Form: GEL
Manufacturer: New Avon LLC
Category: otc | Type: HUMAN OTC DRUG LABEL
Date: 20160217

ACTIVE INGREDIENTS: aluminum zirconium pentachlorohydrate 105 mg/1 mL

Active ingredient
Aluminum Zirconium Pentachlorohydrate (Anhydrous) 10.5% ...

Purpose
...Antiperspirant

Uses

- reduces underarm perspiration
- 24 hour protection

Warnings
For external use only

Do not use on broken skin

Ask a doctor before use if you have kidney disease

Stop use if rash or irritation occurs

Keep out of reach of children. If swallowed, get medical help or contact a Poison Control Center right away.

Directions

- Apply to underarms only.

INACTIVE INGREDIENT

Inactive ingredients: WATER/EAU, GLYCERIN, HELIANTHUS ANNUUS (SUNFLOWER) SEED OIL, STEARETH-2, PPG-15 STEARYL ETHER, SIMMONDSIA CHINENSIS (JOJOBA) SEED OIL, TOCOPHERYL ACETATE, SD ALCOHOL 40-B, STEARETH-20, PARFUM/FRAGRANCE, BENZALKONIUM CHLORIDE.

Questions? 1-800-FOR-AVON